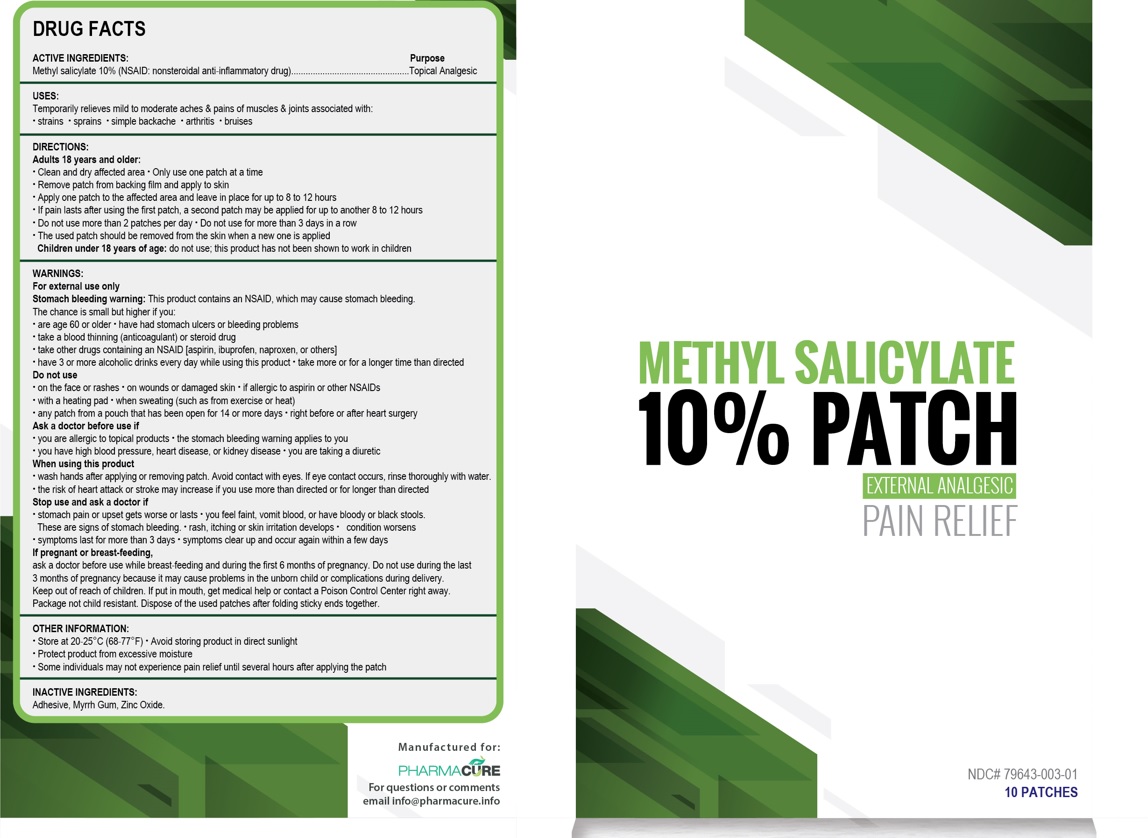 DRUG LABEL: Methyl Salicylate
NDC: 79643-003 | Form: PATCH
Manufacturer: PHARMACURE LLC
Category: otc | Type: HUMAN OTC DRUG LABEL
Date: 20251006

ACTIVE INGREDIENTS: METHYL SALICYLATE 100 mg/1000 mg
INACTIVE INGREDIENTS: MYRRH; ZINC OXIDE

Active Ingredient Purpose

Methyl Salicylate 10% (NSAID: Nonsteroidal anti-inflammatory drug) Topical Analgesic

Uses

Temporarily relieves mild to moderate aches & pains of muscles & joints associated with:

• strains • sprains • simple backache • arthritis • bruises

Warnings

For external use only
Stomach bleeding warning: This product contains an NSAID, which may cause stomach bleeding.
The chance is small but higher if you:

• are age 60 or older • have had stomach ulcers or bleeding problems
• take a blood thinning (anticoagulant) or steroid drug
• take other drugs containing an NSAID (aspirin, ibuprofen, naproxen, or others]
• have 3 or more alcoholic drinks every day while using this product • take more or for a longer time than directed

Do not use

• on the face or rashes • on wounds or damaged skin • if allergic to aspirin or other NSAIDs
• with a heating pad • when sweating (such as from exercise or heat)
• any patch from a pouch that has been open for 14 or more days • right before or after heart surgery

Ask a doctor before use if
• you are allergic to topical products • the stomach bleeding warning applies to you
• you have high blood pressure, heart disease, or kidney disease • you are taking a diuretic

When using this product

• wash hands after applying or removing patch. Avoid contact with eyes. If eye contact occurs, rinse thoroughly with water.
• the risk of heart attack or stroke may increase if you use more than directed or for longer than directed

Stop use and ask a doctor if
• stomach pain or upset gets worse or lasts • you feel faint, vomit blood, or have bloody or black stools
These are signs of stomach bleeding. • rash, itching or skin irritation develops
• condition worsens
• symptoms last for more than 3 days • symptoms clear up and occur again within a few days

If pregnant or breast-feeding,

ask a doctor before use while breast-feeding and during the first 6 months of pregnancy. Do not use during the last 3 months of pregnancy because it may cause problems in the unborn child or complications during delivery.
Keep out of reach of children. If put in mouth, get medical help or contact a Poison Control Center right away. Package not child resistant. Dispose of the used patches after folding sticky ends together.

Directions

Adults 18 years and older:

•Clean and dry affected area • Only use one patch at a time
• Remove patch from backing film and apply to skin
• Apply one patch to the affected area and leave in place for up to 8 to 12 hours
• If pain lasts after using the first patch, a second patch may be applied for up to another 8 to 12 hours

• Do not use more than 2 patches per day • Do not use for more than 3 days in a row
• The used patch should be removed from the skin when a new one is applied
• Children under 18 years of age: do not use: this product has not been shown to work in children

Inactive ingredients

Adhesive, myrrh gum, zinc oxide.

Other information

• Store at 20-25°C (68-77°F) • Avoid storing product in direct sunlight
•Protect product from excessive moisture
•Some individuals may not experience pain relief until several hours after applying the patch